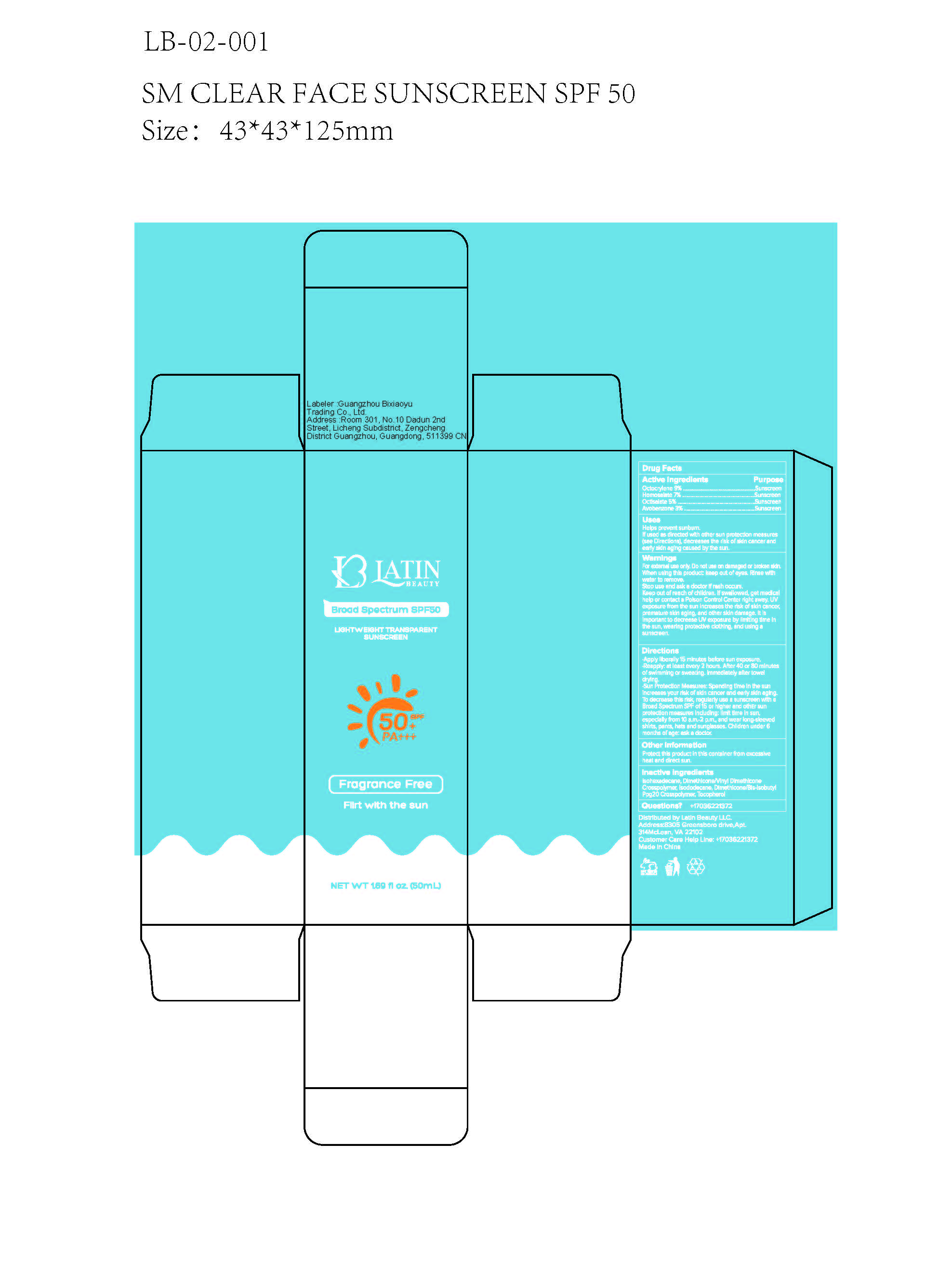 DRUG LABEL: Transparent Gel Sunscreen SPF50, Flirt with the Sun
NDC: 85885-121 | Form: CREAM
Manufacturer: Latin Beauty LLC
Category: otc | Type: HUMAN OTC DRUG LABEL
Date: 20250717

ACTIVE INGREDIENTS: OCTISALATE 5 g/100 mL; HOMOSALATE 7 g/100 mL; OCTOCRYLENE 9 g/100 mL; AVOBENZONE 3 g/100 mL
INACTIVE INGREDIENTS: ISODODECANE; ISOHEXADECANE; DIMETHICONE/VINYL DIMETHICONE CROSSPOLYMER (SOFT PARTICLE); TOCOPHEROL; DIMETHICONE/BIS-ISOBUTYL PPG-20 CROSSPOLYMER

85885-121

ACTIVE INGRENDIENT

Octocrylene
Homosalate
Octisalate
Avobenzone

PURPOSE

Sunscreen

Uses
Helps prevent sunburn.If used as directed with other sun protection measures(see Directions), decreases the risk of skin cancer andearly skin aging caused by the sun.

Stop use and ask a doctor if rash occurs.Keep out of reach of children. lf swallowed, get medicalhelp or contact a Poison Control Center right away. UVexposure from the sun increases the risk of skin cancerpremature skin aging, and other skin damage. lt isimportant to decrease UV exposure by limiting time inthe sun, wearing protective clothing, and using asunscreen.

WARNINGS

WarningsFor extemal use only, Do not use on damaged or broken skin.When using this product: keep out of eyes. Rinse withwater to remove.Stop use and ask a doctor if rash occurs.Keep out of reach of children. lf swallowed, get medicalhelp or contact a Poison Control Center right away. UVexposure from the sun increases the risk of skin cancer,premature skin aging, and other skin damage. lt isimportant to decrease UV exposure by limiting time inthe sun, wearing protective clothing, and using asunscreen.

Directions
Apply liberally 15 minutes before sun exposure..Reapply: at least every 2 hours. After 40 or 80 minutesof swimming or sweating.lmmediately after toweldrying..Sun Protection Measures: Spending time in the sunincreases your risk of skin cancer and early skin agingTo decrease this risk, regularly use a sunscreen with aBroad Spectrum SPF of 15 or higher and othEr sunprotection measures including: limit time in sun,especially from 10 a.m.-2 p.m., and wear long-sleevedshirts, pants, hats and sunglasses. Children under 6months of age: ask a doctor.

DOSAGE AND ADMINISTRATION

Apply liberally 15 minutes before sun exposure.Reapply: at least every 2 hours. After 40 or 80 minutesof swimming or sweating. lmmediately after toweldrying.

Other information
Protect this product in this container from excessiveheat and direct sun.

Keep out of reach of children. lf swallowed, get medicalhelp or contact a Poison Control Center right away.

INACTIVE INGREDIENT

Isohexadecane, Dimethicone/Vinyl DimethiconeCrosspolymer, lsododecane, Dimethicone/Bis-sobutyPpg20 Crosspolymer, Tocopherol